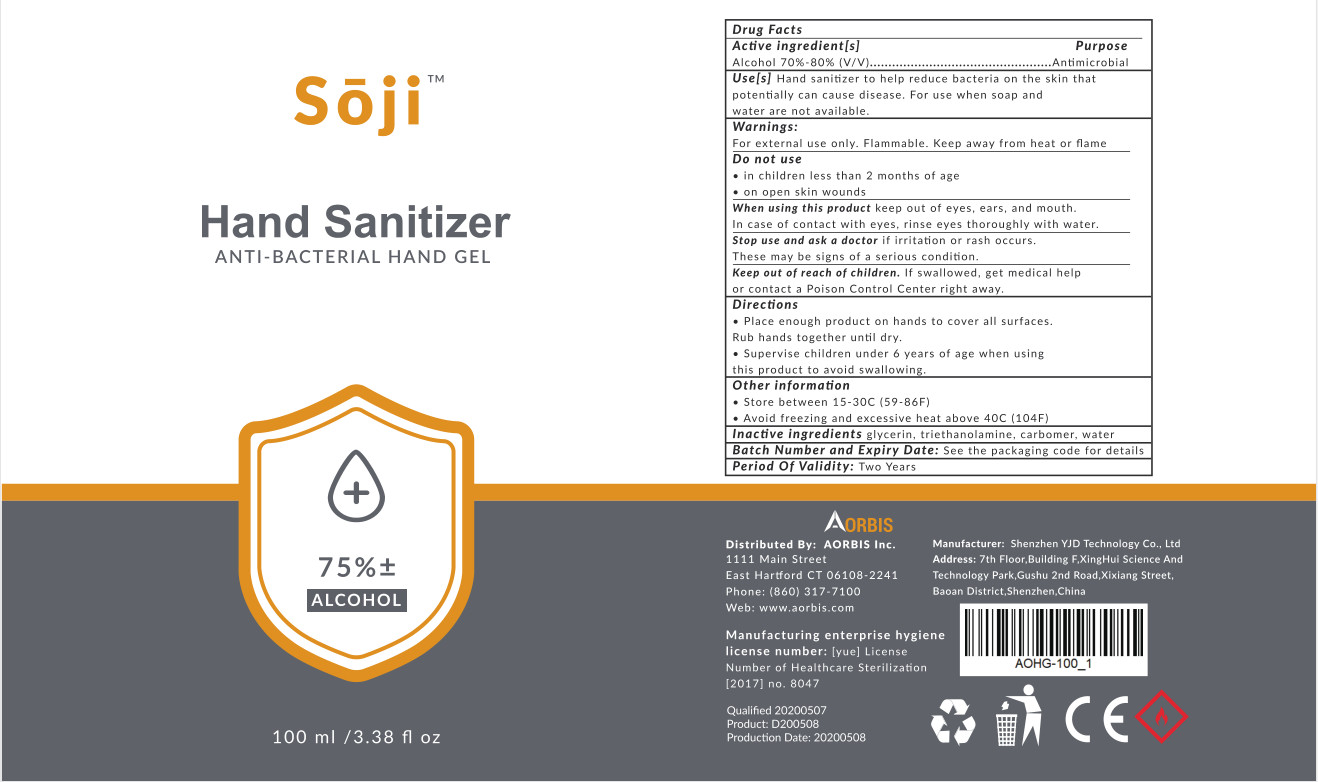 DRUG LABEL: hand sanitizer
NDC: 54493-004 | Form: LIQUID
Manufacturer: Shenzhen YJD Technology Co., Ltd.
Category: otc | Type: HUMAN OTC DRUG LABEL
Date: 20200514

ACTIVE INGREDIENTS: ALCOHOL 75 mL/100 mL
INACTIVE INGREDIENTS: TROLAMINE; WATER; GLYCERIN; CARBOMER HOMOPOLYMER, UNSPECIFIED TYPE

DOSAGE AND ADMINISTRATION

1.Store between 15-30°C (59-86°F)
2.Avoid freezing and excessive heat above 40°C (104°F)

INACTIVE INGREDIENT

Water

Glycerin

Carbomer

Triethanolamine

INDICATIONS AND USAGE

1.Place enough product on hands to cover all surfaces.Rub hands together until dry.
2.Supervise children under 6 years of age when using this product to avoid swallowing.

ACTIVE INGREDIENT

Alcohol

PURPOSE

Disinfection
Sterilization

keep out of reach of children

WARNINGS

For external use only. Flammable. Keep away from heat or flame